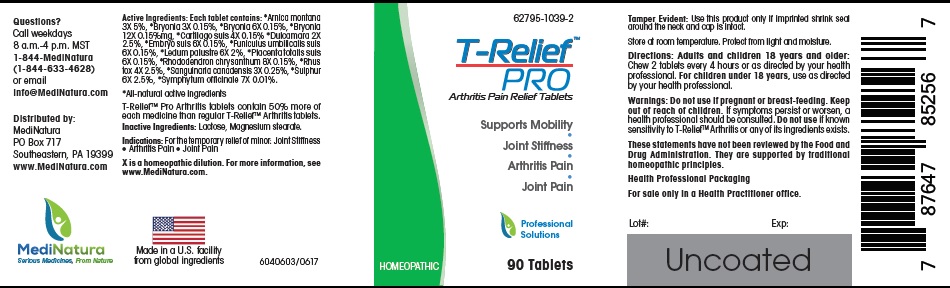 DRUG LABEL: T-Relief PRO Arthritis
NDC: 62795-1039 | Form: TABLET
Manufacturer: MediNatura Inc
Category: homeopathic | Type: HUMAN OTC DRUG LABEL
Date: 20210629

ACTIVE INGREDIENTS: ARNICA MONTANA 3 [hp_X]/1 1; BRYONIA ALBA WHOLE 3 [hp_X]/1 1; SUS SCROFA CARTILAGE 4 [hp_X]/1 1; SOLANUM DULCAMARA TOP 2 [hp_X]/1 1; SUS SCROFA EMBRYO 6 [hp_X]/1 1; SUS SCROFA UMBILICAL CORD 6 [hp_X]/1 1; RHODODENDRON TOMENTOSUM LEAFY TWIG 6 [hp_X]/1 1; SUS SCROFA PLACENTA 6 [hp_X]/1 1; RHODODENDRON AUREUM LEAF 8 [hp_X]/1 1; TOXICODENDRON PUBESCENS LEAF 4 [hp_X]/1 1; SANGUINARIA CANADENSIS ROOT 3 [hp_X]/1 1; SULFUR 6 [hp_X]/1 1; COMFREY ROOT 7 [hp_X]/1 1
INACTIVE INGREDIENTS: LACTOSE, UNSPECIFIED FORM; MAGNESIUM STEARATE

T-Relief PRO Arthritis

WARNINGS

Do not use If pregnant or breast-feeding. Keep out of reach of children. If symptoms persist or worsen, a health professional should be consulted. Do not use if known sensitivity to T-Relief Arthritis or any of its ingredients exists.

INGREDIENTS

Arnica montana 3X 5%, Bryonia alba 3X 0.15%, Bryonia alba 6X 0.15%, Bryonia alba 12X 0.15% mg., Cartilago suis 4X 0.15%, Dulcamara 2X 2.5%, Embryo suis 6X 0.15%, Funiculus umbilicalis suis 6X 0.15%, Ledum palustre 6X 2%, Placenta lolasis suis 6X 0.15%, Rhododendron chrysanthum 8X 0.15%, Rhus toxicodendron 4X 2.5%, Sanguinaria canadensis 3X 0.25%, Sulphur 6X 2.5%, . Symphytum officinale 7X 0.01%.

USES

Arthritis Pain relief tablets
• Supports Mobility
• Joint Stiffness
• Arthritis Pain
• Joint Pain

INACTIVE INGREDIENT

Lactose, Magnesium stearate

INDICATIONS

For the temporary relief of minor Joint Stiffness, Arthritis Pain, Joint Pain.

DIRECTIONS

Adults : Chew 2 tablet every 4 hours or as directed by health professional. For Children under 18 years, use as directed by health professional

KEEP OUT OF REACH OF CHILDREN